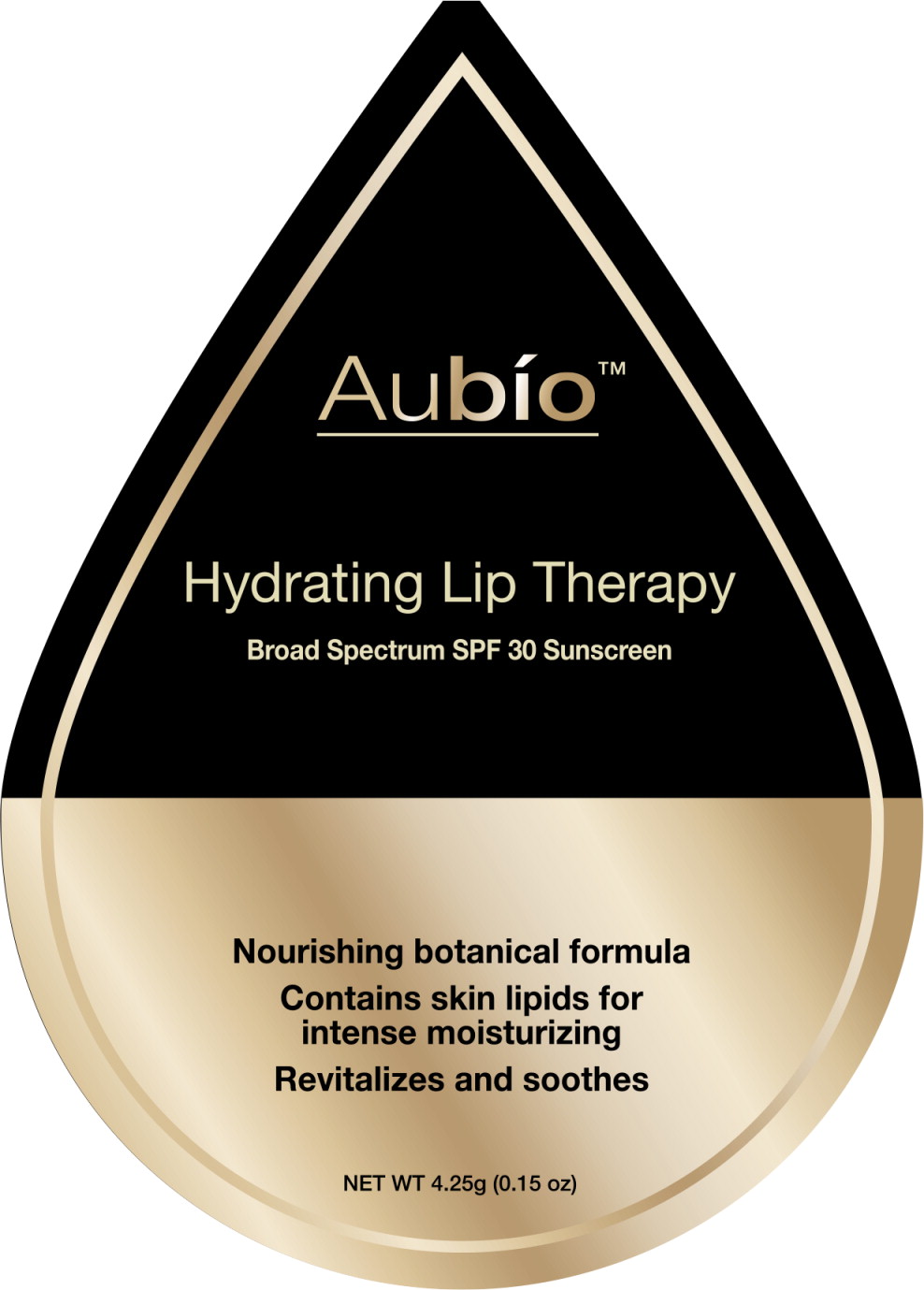 DRUG LABEL: Aubio Life Sciences Lip
NDC: 70365-002 | Form: LIPSTICK
Manufacturer: Aubio Life Sciences LLC
Category: otc | Type: HUMAN OTC DRUG LABEL
Date: 20160131

ACTIVE INGREDIENTS: Homosalate 150 mg/1 g; Avobenzone 30 mg/1 g; Octisalate 30 mg/1 g; Octocrylene 27 mg/1 g
INACTIVE INGREDIENTS: Water; Glycerin; Carbomer Interpolymer Type A (allyl sucrose crosslinked); Glycyrrhizinate Dipotassium; Phytosphingosine; Sodium Lauroyl Lactylate; Xanthan Gum; Cholesterol; Ceramide NP; 3-DEHYDROXY CERAMIDE 1; Ceramide AP; Shea Butter; Coconut Oil; Bis-Diglyceryl Polyacyladipate-2; Medium-Chain Triglycerides; Yellow Wax; Ceresin; Isohexadecane; Carnauba Wax; Candelilla Wax; Lavandula Angustifolia Flower; Melissa Officinalis; Zanthoxylum Bungeanum Fruit; Bilberry Seed Oil; Sunflower Oil; Sarracenia Purpurea; Raspberry; Mango; Cucumber

Drug Facts

Active Ingredients

Homosalate 15.00%

Octisalate 5.00%

Avobenzene 3.00%

Octocrylene 2.70%

Purpose

Sunscreen

Sunscreen

Sunscreen

Sunscreen

Uses

- Helps prevent sunburn
- If used as directed with other sun protection measures (see Directions), decreases the risk of skin cancer and early skin aging caused by the sun

Warnings

For external use only

Do not use on damaged or broken skin

When using this product

- keep out of eyes. Rinse with water to remove

Stop use and ask a doctor if rash occurs

Keep out of reach of children. If swallowed, get medical help or contact a Poison Control Center immediately

Directions

- Apply generously and evenly 15 minutes before sun exposure
- Children under 6 months of age; ask a doctor
- Sun protection measures. Spending time in the sun increases your risk of skin cancer and early skin aging. To decrease this risk, regularly use a BROAD SPECTRUM SPF value of 15 or higher and other sun protection measures including:
  - limit time in the sun, especially between 10am to 2pm
  - Wear long sleeve shirts, pants, hats, and sunglasses
  - Reapply at least every 2 hours
  - Use a water-resistant sunscreen if swimming or sweating

Inactive Ingredients

Butyrospermum Parkii (Shea) Butter, Cocos Nucifera (Coconut) Oil, Bis-Diglyceryl Polycyladipate-2, Caprylic/Capric Triglyceride, Beeswax, Ozokerite, Polyisobutene, Copernicia Cerifera (Carnauba Wax), Euphorbia Cerifera (Candelila) Wax, Sarracenia Leucophylla Leaf/Stem/Flower/Seed Extract (and) Sarracenia Purpurea Leaf/Stem/Flower/Seed Extract, Lavandula Augustifolia (Lavender) Flower Extract Melissa Officinalis (Balm Mint) Extract Zanthoxylum Bungeanum Fruit Extract Vaccinium Myrtillus Seed Oil, Helianthus Annuus (Sunflower) Seed Oil, Unsaponifiables, Dipotassium Glycyrrtiizate) Phytosphingosine, Ceramide AP, Ceramide EOP, Ceramide NP, Giycerin, Water (Aqua), Cholesterol, Sodium Lauroyi Lactylate, Carbomer, Xantham Gum, Flavor

Other Information

- Recap after each use
- Store at room temperature
- Protect the product in this container from excessive heat and direct sun

Questions or comments?

Call Toll-free 1 -844-My-Aubío

(1-844-692-8246)

Weekdays 9am-5pm PT. If you are not completely satisfied, save receipt and remaining product and call us.

Principal Display Panel - Blister Pack Label

Aubío™

Hydrating Lip Therapy

Broad Spectrum SPF 30 Sunscreen

Nourishing botanical formula

Contains skin lipids for
intense moisturizing

Revitalizes and soothes

NET WT 4.25g (0.15 oz)